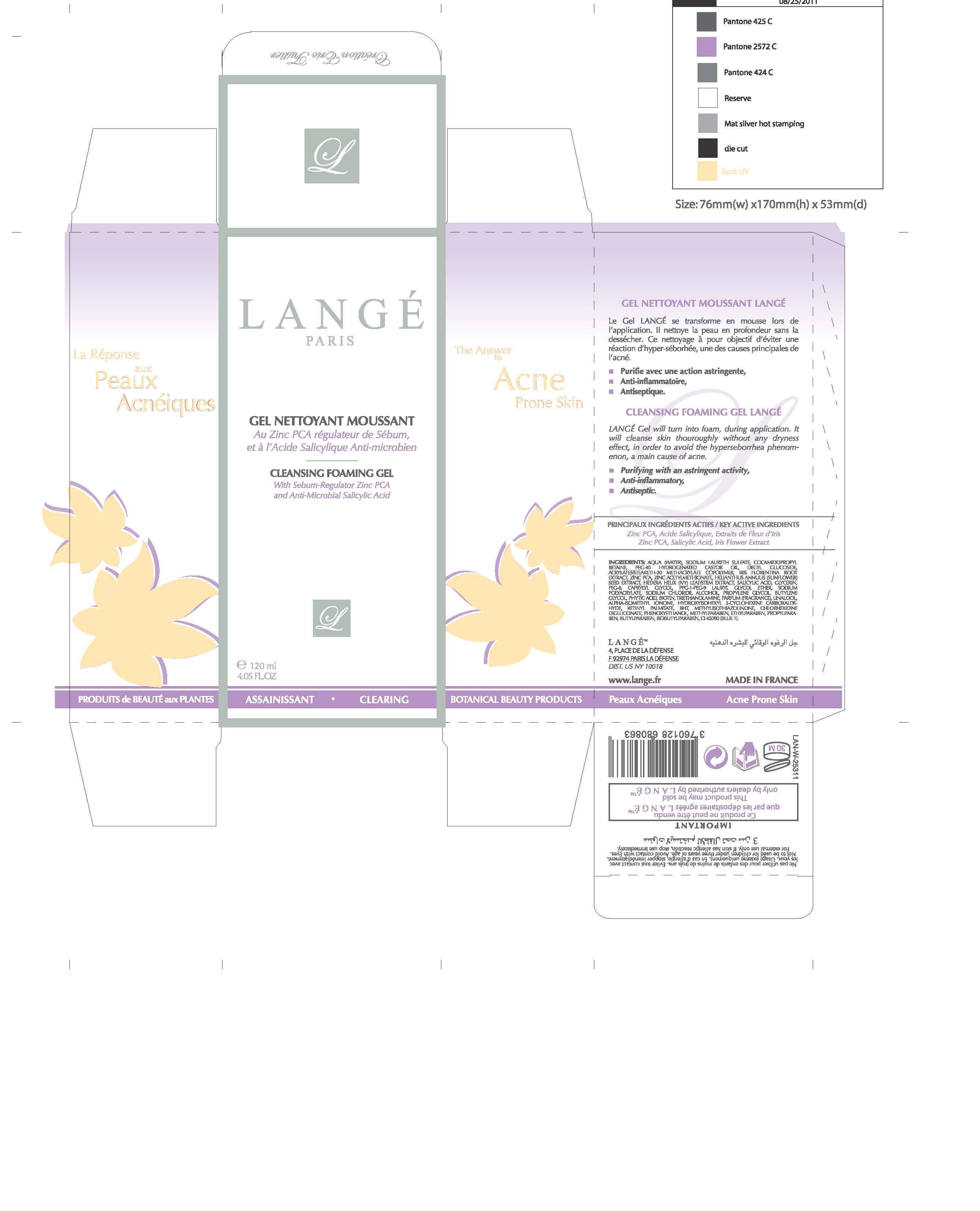 DRUG LABEL: Cleansing Foaming Gel
NDC: 51830-053 | Form: GEL
Manufacturer: LANGE SAS
Category: otc | Type: HUMAN OTC DRUG LABEL
Date: 20120718

ACTIVE INGREDIENTS: ZINC PIDOLATE .072 mg/120 mg; SALICYLIC ACID 12 mg/120 mg; IRIS GERMANICA VAR. FLORENTINA ROOT 1.8 mg/120 mg
INACTIVE INGREDIENTS: WATER; SODIUM LAURETH SULFATE; COCAMIDOPROPYL BETAINE; DECYL GLUCOSIDE; ZINC ACETYLMETHIONATE; SUNFLOWER SEED; HEDERA HELIX LEAF; GLYCERIN; POLYETHYLENE GLYCOL 400; CAPRYLYL GLYCOL; SODIUM POLYACRYLATE (8000 MW); SODIUM CHLORIDE; ALCOHOL; PROPYLENE GLYCOL; BUTYLENE GLYCOL; FYTIC ACID; BIOTIN; TROLAMINE; LINALOOL, (+/-)-; ISOMETHYL-.ALPHA.-IONONE; HYDROXYISOHEXYL 3-CYCLOHEXENE CARBOXALDEHYDE; BUTYLATED HYDROXYTOLUENE; METHYLISOTHIAZOLINONE; CHLORHEXIDINE GLUCONATE; PHENOXYETHANOL; METHYLPARABEN; BUTYLPARABEN; ETHYLPARABEN; PROPYLPARABEN; ISOBUTYLPARABEN; VITAMIN A PALMITATE; POLYOXYL 40 HYDROGENATED CASTOR OIL

Key Active Ingredients
Zinc PCA, Salicylic Acid, Iris Flower Extract

PURPOSE

The Answer to Acne Prone Skin
Cleansing Foaming Gel Lange

- Purifying with an astingent activity,
- Anti-inflammatory,
- Antiseptic

Keep out of reach of children.

INDICATIONS AND USAGE

Lange Gel will turn into foam, during application. It will cleanse skin thoroughly without any dryness effect, in order to avoid hyperseboohea phenomenon, a main cause of acne.

Warnings

DOSAGE AND ADMINISTRATION

120 mL / 4.05 FL OZ.

INACTIVE INGREDIENT

Ingredients:AQUA,SODIUM LAURETH SULFATE, COCAMIDOPROPYL BETAINE, PEG-40 HYDROGENATED CASTOR OIL DECYL GLUCOSIDE, ACRYLATES/STEARETH-20 METHACRYLATE COPOLYMER, IRIS FLORENTINA ROOT EXTRACT, ZINC PCA, ZINC ACETYLMETHIONATE, HELIANTHUS ANNUUS SEED EXTRACT, HEDERA HELIX LEAF/STEM EXTRACT,SALICYLIC ACID, GLYCERIN,PEG-8, CAPRYLYL GLYCOL,PPG-1-PEG-9 LAURYL GLYCOL ETHER,SODIUM POLYACRYLATE,SODIUM CHLORIDE,ALCOHOL,PROPYLENE GLYCOL,BUTYLENE GLYCOL,PHYTIC ACID,BIOTIN,TRIETHANOLAMINE,PARFUM,LINALOOL,ALPHA-ISOMETHYL IONONE, HYDROXYISOHEXYL 3-CYCLOHEXENE CARBOXALDEHYDE,RETINYL PALMITATE,BHT,METHYLISOTHIAZOLINONE,CHLORHEXIDINE DIGLUCONATE,PHENOXYETHANOL,METHYLPARABEN,BUTYLPARABEN, ETHYLPARABEN,PROPYLPARABEN,ISOBUTYLPARABEN,CI 42090 (BLUE 1)